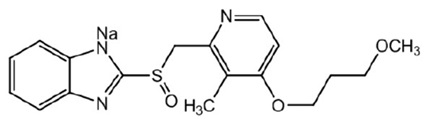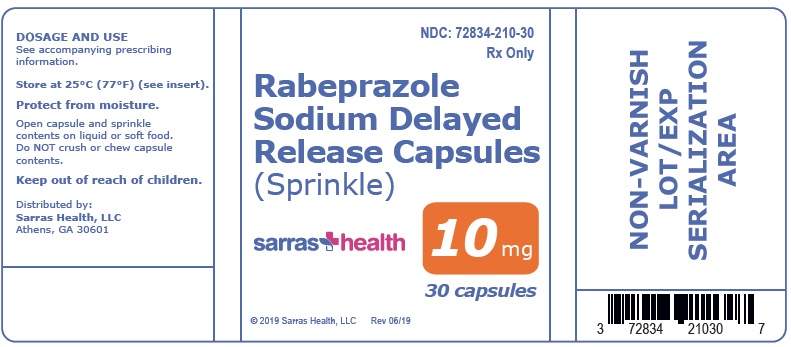 DRUG LABEL: rabeprazole sodium delayed-release
NDC: 72834-210 | Form: CAPSULE, DELAYED RELEASE
Manufacturer: Sarras Health, LLC
Category: prescription | Type: HUMAN PRESCRIPTION DRUG LABEL
Date: 20201229

ACTIVE INGREDIENTS: RABEPRAZOLE SODIUM 10 mg/1 1
INACTIVE INGREDIENTS: SILICON DIOXIDE; DIACETYLATED MONOGLYCERIDES; ETHYLCELLULOSES; HYDROXYPROPYL CELLULOSE (1600000 WAMW); HYPROMELLOSE PHTHALATE (24% PHTHALATE, 55 CST); MAGNESIUM OXIDE; MAGNESIUM STEARATE; MANNITOL; TALC; TITANIUM DIOXIDE; CARRAGEENAN; POTASSIUM CHLORIDE; FD&C YELLOW NO. 6

HIGHLIGHTS OF PRESCRIBING INFORMATION

These highlights do not include all the information needed to use RABEPRAZOLE SODIUM DELAYED-RELEASE CAPSULES safely and effectively. See full prescribing information for RABEPRAZOLE SODIUM DELAYED-RELEASE CAPSULES.
Rabeprazole Sodium Delayed-Release Capsules (Sprinkle), for oral use
Initial U.S. Approval: 1999

RECENT MAJOR CHANGES

Warnings and Precautions, Fundic Gland Polyps (5.10) 06/2018

1 INDICATIONS AND USAGE

Rabeprazole sodium delayed-release capsules are a proton-pump inhibitor (PPI) indicated for the treatment of Gastroesophageal Reflux Disease (GERD) in pediatric patients 1 to 11 years of age (1).

2 DOSAGE AND ADMINISTRATION

Dosage Regimen (2.1):

The recommended dosage in pediatric patients 1 to 11 years of age for up to 12 weeks is:

- Less than 15 kg: 5 mg once daily with the option to increase to 10 mg once daily, if inadequate response
- 15 kg or more: 10 mg once daily

Administration Recommendations (2.2):

- Take dose 30 minutes before a meal
- Do not swallow the capsule whole
- Open a rabeprazole sodium delayed-release capsule and sprinkle granule contents on a spoonful of soft food or liquid (e.g., applesauce). Food or liquid should be at or below room temperature.
- Do not chew or crush the granules
- Take entire dose within 15 minutes of preparation

3 DOSAGE FORMS AND STRENGTHS

Delayed-Release Capsules: 10 mg (3).

4 CONTRAINDICATIONS

- Patients with a history of hypersensitivity to rabeprazole (4).
- PPIs, including rabeprazole sodium delayed-release capsules, are contraindicated in patients receiving rilpivirine-containing products (4, 7).

5 WARNINGS AND PRECAUTIONS

- Gastric Malignancy: In adults, symptomatic response to therapy with rabeprazole does not preclude the presence of gastric malignancy. Consider additional follow-up and diagnostic testing (5.1).
- Use with Warfarin: Monitor for increases in INR and prothrombin time (5.2, 7).
- Acute Interstitial Nephritis: Observed in patients taking PPIs (5.3).
- Clostridium difficile-Associated Diarrhea: PPI therapy may be associated with increased risk (5.4).
- Bone Fracture: Long-term and multiple daily dose PPI therapy may be associated with an increased risk for osteoporosis-related fractures of the hip, wrist, or spine (5.5).
- Cutaneous and Systemic Lupus Erythematosus: Mostly cutaneous; new onset or exacerbation of existing disease; discontinue rabeprazole sodium delayed-release capsules and refer to specialist for evaluation (5.6).
- Cyanocobalamin (Vitamin B-12) Deficiency: Daily long-term use (e.g., longer than 3 years) may lead to malabsorption or a deficiency of cyanocobalamin (5.7).
- Hypomagnesemia: Reported rarely with prolonged treatment with PPIs (5.8).
- Interaction with Methotrexate: Concomitant use with PPIs may elevate and/or prolong serum concentrations of methotrexate and/or its metabolite, possibly leading to toxicity. With high dose methotrexate administration, consider a temporary withdrawal of rabeprazole sodium delayed-release capsules (5.9, 7).
- Fundic Gland Polyps: Risk increases with long-term use, especially beyond one year. Use the shortest duration of therapy (5.10).

6 ADVERSE REACTIONS

Most common adverse reactions (>5%) are vomiting, abdominal pain, diarrhea, headache, and nausea (6.1).

To report SUSPECTED ADVERSE REACTIONS, contact Sarras Health, LLC at 888-570-5004 or FDA at 1-800-FDA-1088 or www.fda.gov/medwatch

7 DRUG INTERACTIONS

See full prescribing information for a list of clinically important drug interactions (7).

8 USE IN SPECIFIC POPULATIONS

Pediatric Use: Use is not recommended for the treatment of GERD in pediatric patients younger than 1 year of age; efficacy not demonstrated (8.4).

FULL PRESCRIBING INFORMATION

1 INDICATIONS AND USAGE

Rabeprazole sodium delayed-release capsules are indicated for treatment of Gastroesophageal Reflux Disease (GERD) in pediatric patients 1 to 11 years of age for up to 12 weeks.

2 DOSAGE AND ADMINISTRATION

2.1 Dosage Regimen

Rabeprazole sodium delayed-release capsules are recommended for up to 12 weeks in pediatric patients 1 to 11 years of age and is dosed by body weight:

- Less than 15 kg: 5 mg once daily with the option to increase to 10 mg once daily, if inadequate response.
- 15 kg or more: 10 mg once daily.

2.2 Administration Recommendations

- Take the dose 30 minutes before a meal.
- Do not swallow the capsule whole.
- Open a capsule and sprinkle entire contents on a small amount of soft food (e.g., applesauce, fruit or vegetable based baby food, or yogurt) or empty contents into a small amount of liquid (e.g., infant formula, apple juice, or pediatric electrolyte solution). Food or liquid should be at or below room temperature.
- Do not chew or crush the granules.
- Take the entire dose within 15 minutes of preparation.
- Do not store mixture for future use.
- Take a missed dose as soon as possible. If it is almost time for the next dose, skip the missed dose and go back to the normal schedule. Do not take 2 doses at the same time.

3 DOSAGE FORMS AND STRENGTHS

Rabeprazole sodium delayed-release capsules (sprinkle) are provided as:

- 10 mg: transparent yellow and opaque white No. 2 capsule imprinted with "↑" on the capsule cap and "ACX 10mg" on the capsule body.

4 CONTRAINDICATIONS

- Rabeprazole sodium delayed-release capsules are contraindicated in patients with known hypersensitivity to rabeprazole, substituted benzimidazoles, or to any component of the formulation. Hypersensitivity reactions may include anaphylaxis, anaphylactic shock, angioedema, bronchospasm, acute interstitial nephritis, and urticaria [see Adverse Reactions (6)].
- PPIs, including rabeprazole sodium delayed-release capsules, are contraindicated with rilpivirine-containing products [see Drug Interactions (7)].

5 WARNINGS AND PRECAUTIONS

5.1 Presence of Gastric Malignancy

In adults, symptomatic response to therapy with rabeprazole sodium delayed-release capsules does not preclude the presence of gastric malignancy. Consider additional follow-up and diagnostic testing in adult patients who have a suboptimal response or an early symptomatic relapse after completing treatment with a PPI. In older patients, also consider an endoscopy.

5.2 Interaction with Warfarin

Steady state interactions of rabeprazole and warfarin have not been adequately evaluated in patients. There have been reports of increased INR and prothrombin time in patients receiving a proton pump inhibitor and warfarin concomitantly. Increases in INR and prothrombin time may lead to abnormal bleeding and even death. Patients treated with rabeprazole sodium delayed-release capsules and warfarin concomitantly may need to be monitored for increases in INR and prothrombin time [see Drug Interactions (7)].

5.3 Acute Interstitial Nephritis

Acute interstitial nephritis has been observed in patients taking PPIs including rabeprazole sodium. Acute interstitial nephritis may occur at any point during PPI therapy and is generally attributed to an idiopathic hypersensitivity reaction. Discontinue rabeprazole sodium delayed-release capsules if acute interstitial nephritis develops [see Contraindications (4)].

5.4 Clostridium difficile-Associated Diarrhea

Published observational studies suggest that PPI therapy like rabeprazole sodium delayed-release capsules may be associated with an increased risk of Clostridium difficile-associated diarrhea, especially in hospitalized patients. This diagnosis should be considered for diarrhea that does not improve [see Adverse Reactions (6.2)].

Patients should use the lowest dose and shortest duration of PPI therapy appropriate to the condition being treated.

Clostridium difficile-associated diarrhea (CDAD) has been reported with use of nearly all antibacterial agents.

5.5 Bone Fracture

Several published observational studies in adults suggest that PPI therapy may be associated with an increased risk for osteoporosis-related fractures of the hip, wrist, or spine. The risk of fracture was increased in patients who received high-dose, defined as multiple daily doses, and long-term PPI therapy (a year or longer). Patients should use the lowest dose and shortest duration of PPI therapy appropriate to the condition being treated.

Patients at risk for osteoporosis-related fractures should be managed according to established treatment guidelines [see Dosage and Administration (2), Adverse Reactions (6.2)].

Rabeprazole sodium delayed-release capsules are indicated for short-term treatment up to 12 weeks. Treatment for longer than 12 weeks is not recommended.

5.6 Cutaneous and Systemic Lupus Erythematosus

Cutaneous lupus erythematosus (CLE) and systemic lupus erythematosus (SLE) have been reported in patients taking PPIs, including rabeprazole. These events have occurred as both new onset and an exacerbation of existing autoimmune disease. The majority of PPI-induced lupus erythematosus cases were CLE.

The most common form of CLE reported in patients treated with PPIs was subacute CLE (SCLE) and occurred within weeks to years after continuous drug therapy in patients ranging from infants to the elderly. Generally, histological findings were observed without organ involvement.

Systemic lupus erythematosus (SLE) is less commonly reported than CLE in patients receiving PPIs. PPI associated SLE is usually milder than non-drug induced SLE. Onset of SLE typically occurred within days to years after initiating treatment primarily in patients ranging from young adults to the elderly. The majority of patients presented with rash; however, arthralgia and cytopenia were also reported.

Avoid administration of PPIs for longer than medically indicated. If signs or symptoms consistent with CLE or SLE are noted in patients receiving rabeprazole sodium delayed-release capsules, discontinue the drug and refer the patient to the appropriate specialist for evaluation. Most patients improve with discontinuation of the PPI alone in 4 to 12 weeks. Serological testing (e.g. ANA) may be positive and elevated serological test results may take longer to resolve than clinical manifestations.

5.7 Cyanocobalamin (Vitamin B-12) Deficiency

Daily treatment with any acid-suppressing medications over a long period of time (e.g., longer than 3 years) may lead to malabsorption of cyanocobalamin (vitamin B-12) caused by hypo- or achlorhydria. Rare reports of cyanocobalamin deficiency occurring with acid-suppressing therapy have been reported in the literature. This diagnosis should be considered if clinical symptoms consistent with cyanocobalamin deficiency are observed in patients treated with rabeprazole sodium delayed-release capsules.

5.8 Hypomagnesemia

Hypomagnesemia, symptomatic and asymptomatic, has been reported rarely in adult patients treated with PPIs for at least three months, in most cases after a year of therapy. Serious adverse events include tetany, arrhythmias, and seizures. In most patients, treatment of hypomagnesemia required magnesium replacement and discontinuation of the PPI.

For patients expected to be on prolonged treatment or who take PPIs with medications such as digoxin or drugs that may cause hypomagnesemia (e.g., diuretics), healthcare professionals may consider monitoring magnesium levels prior to initiation of PPI treatment and periodically [see Adverse Reactions (6.2)].

Rabeprazole sodium delayed-release capsules are indicated for short-term treatment of up to 12 weeks. Treatment for longer than 12 weeks is not recommended.

5.9 Interaction with Methotrexate

Literature suggests that concomitant use of PPIs with methotrexate (primarily at high dose; see methotrexate prescribing information) may elevate and prolong serum levels of methotrexate and/or its metabolite, possibly leading to methotrexate toxicities. In high-dose methotrexate administration, a temporary withdrawal of the PPI may be considered in some patients [see Drug Interactions (7)].

5.10 Fundic Gland Polyps

PPI use is associated with an increased risk of fundic gland polyps that increases with long-term use, especially beyond one year. Most PPI users who developed fundic gland polyps were asymptomatic and fundic gland polyps were identified incidentally on endoscopy. Use the shortest duration of PPI therapy appropriate to the condition being treated.

6 ADVERSE REACTIONS

The following serious adverse reactions are described below and elsewhere in labeling:

- Acute Interstitial Nephritis [see Warnings and Precautions (5.3)]
- Clostridium difficile-Associated Diarrhea [see Warnings and Precautions (5.4)]
- Bone Fracture [see Warnings and Precautions (5.5)]
- Cutaneous and Systemic Lupus Erythematosus [see Warnings and Precautions (5.6)]
- Cyanocobalamin (Vitamin B-12) Deficiency [see Warnings and Precautions (5.7)]
- Hypomagnesemia [see Warnings and Precautions (5.8)]
- Fundic Gland Polyps [see Warnings and Precautions (5.10)]

6.1 Clinical Studies Experience

Because clinical trials are conducted under varying conditions, adverse reaction rates observed in the clinical trials of a drug cannot be directly compared to rates in the clinical trials of another drug and may not reflect the rates observed in practice.

The efficacy of rabeprazole sodium delayed-release capsules was established in a two-part, randomized, multicenter, double-blind, parallel-group study of 127 pediatric patients 1 to 11 years of age with a history of at least one GERD symptom within the 3 months before screening and a positive esophagogastroduodenoscopy (EGD; Hetzel-Dent Endoscopic Classification System, Grade ≥1 and Histological Features of Reflux Esophagitis Scale, Grade >0). The two-part study consisted of a 12-week treatment period in patients with endoscopically-proven GERD followed by a 24-week, double-blinded extension study. Subjects had a mean age of 6 years (range: 1 to 11 years) and 44% (56/127) were female and 56% (71/127) were male. Of the 127 subjects enrolled, 78% (99/127) were white, 10% (13/127) were black, and 2% (3/127) were Asian.

In the study, patients less than 15 kg body weight received either 5 mg or 10 mg rabeprazole sodium delayed-release capsules and patients 15 kg or greater body weight received 10 mg rabeprazole sodium delayed-release capsules. In this study, some patients were treated for 36 weeks. The most common adverse reactions leading to discontinuation were vomiting, abdominal pain, diarrhea, and nausea. The most common adverse reactions from the first 12 weeks of treatment are listed in Table 1.

Table 1: Common Adverse Reactions* in Pediatric Study (Ages 1 To 11 Years First 12 Weeks of Treatment)
Adverse Reaction | Patients Less than 15 kg |  | Patients 15 kg or greater
 | 5 mg (N=21) % | 10 mg (N=19) % | 10 mg (N=44) %
Vomiting | 10 | 11 | 14
Abdominal Pain | 0 | 0 | 16
Diarrhea | 14 | 21 | 9
Headache | 0 | 0 | 9
Nausea | 0 | 0 | 9
* incidence of adverse reactions ≥9%

The safety profile was similar for those patients who received treatment for up to 36 weeks.

Adults and Adolescents Experience with Other Rabeprazole Formulations

The data described below reflect exposure to rabeprazole sodium delayed-release tablets in 1064 adult patients exposed for up to 8 weeks. The studies were primarily placebo- and active-controlled trials in adult patients with Erosive or Ulcerative Gastroesophageal Reflux Disease (GERD), Duodenal Ulcers and Gastric Ulcers. The population had a mean age of 53 years (range 18-89 years) and had a ratio of approximately 60% male: 40% female. The racial distribution was 86% Caucasian, 8% African American, 2% Asian, and 5% other. Most patients received either 10 mg, 20 mg, or 40 mg per day of rabeprazole.

An analysis of adverse reactions appearing in ≥2% of rabeprazole-treated patients (n=1064) and with a greater frequency than placebo (n=89) in controlled North American and European acute treatment trials, revealed the following adverse reactions: pain (3% vs. 1%), pharyngitis (3% vs. 2%), flatulence (3% vs. 1%), infection (2% vs. 1%), and constipation (2% vs. 1%).

Other adverse reactions seen in controlled clinical trials, which do not meet the above criteria (≥2% of rabeprazole-treated patients and greater than placebo) and for which there is a possibility of a causal relationship to rabeprazole, include the following: headache, abdominal pain, diarrhea, dry mouth, dizziness, peripheral edema, hepatic enzyme increase, hepatitis, hepatic encephalopathy, myalgia, and arthralgia.

In a multicenter, open-label study of adolescent patients 12 to 16 years of age with a clinical diagnosis of symptomatic GERD or endoscopically proven GERD, the adverse event profile was similar to that of adults. The adverse reactions reported without regard to relationship to rabeprazole that occurred in ≥2% of 111 patients were headache (9.9%), diarrhea (4.5%), nausea (4.5%), vomiting (3.6%), and abdominal pain (3.6%). The related reported adverse reactions that occurred in ≥2% of patients were headache (5.4%) and nausea (1.8%). There were no adverse reactions reported in this study that were not previously observed in adults.

6.2 Postmarketing Experience

The following adverse reactions have been identified during post approval use of rabeprazole sodium. Because these reactions are reported voluntarily from a population of uncertain size, it is not always possible to reliably estimate their frequency or establish a causal relationship to drug exposure.

Blood and Lymphatic System Disorders: agranulocytosis, hemolytic anemia, leukopenia, pancytopenia, and thrombocytopenia
Ear and Labyrinth Disorders: vertigo
Eye Disorders: blurred vision
Gastrointestinal Disorders: fundic gland polyps
General Disorders and Administration Site Conditions: sudden death
Hepatobiliary Disorders: jaundice
Immune System Disorders: anaphylaxis, angioedema, systemic lupus erythematosus, Stevens-Johnson syndrome, toxic epidermal necrolysis (some fatal)
Infections and Infestations: Clostridium difficile-associated diarrhea
Investigations: Increases in prothrombin time/INR (in patients treated with concomitant warfarin), TSH elevations
Metabolism and Nutrition Disorders: hyperammonemia, hypomagnesemia
Musculoskeletal System Disorders: bone fracture, rhabdomyolysis
Nervous System Disorders: coma
Psychiatric Disorders: delirium, disorientation
Renal and Urinary Disorders: interstitial nephritis
Respiratory, Thoracic and Mediastinal Disorders: interstitial pneumonia
Skin and Subcutaneous Tissue Disorders: severe dermatologic reactions, including bullous and other drug eruptions of the skin; cutaneous lupus erythematosus, erythema multiforme

7 DRUG INTERACTIONS

Table 2 includes clinically important drug interactions and interaction with diagnostics when administered concomitantly with rabeprazole sodium delayed-release capsules and instructions for preventing or managing them.

Consult the labeling of concomitantly used drugs to obtain further information about interactions with PPIs.

Table 2: Clinically Relevant Interactions Affecting Drugs Co-Administered with Rabeprazole Sodium Delayed-Release Capsules and Interactions with Diagnostics
Antiretrovirals
Clinical Impact: | The effect of PPIs on antiretroviral drugs is variable. The clinical importance and the mechanisms behind these interactions are not always known.; - Decreased exposure of some antiretroviral drugs (e.g., rilpivirine, atazanavir, nelfinavir) when used concomitantly with rabeprazole may reduce antiviral effect and promote the development of drug resistance - Increased exposure of other antiretroviral drugs (e.g., saquinavir) when used concomitantly with rabeprazole may increase toxicity. - There are other antiretroviral drugs which do not result in clinically relevant interactions with rabeprazole.
Intervention: | Rilpivirine-containing products: Concomitant use with rabeprazole sodium delayed-release capsules is contraindicated [see Contraindications (4)]. See prescribing information.
Intervention: | Atazanavir: See prescribing information for atazanavir for dosing information.
Intervention: | Nelfinavir: Avoid concomitant use with rabeprazole sodium delayed-release capsules. See prescribing information for nelfinavir.
Intervention: | Saquinavir: See the prescribing information for saquinavir and monitor for potential saquinavir toxicities.
Intervention: | Other antiretrovirals: See prescribing information.
Warfarin
Clinical Impact: | Increased INR and prothrombin time in patients receiving PPIs, including rabeprazole, and warfarin concomitantly. Increases in INR and prothrombin time may lead to abnormal bleeding and even death [see Warnings and Precautions (5.2)].
Intervention: | Monitor INR and prothrombin time. Dose adjustment of warfarin may be needed to maintain target INR range. See prescribing information for warfarin.
Methotrexate
Clinical Impact: | Concomitant use of rabeprazole with methotrexate (primarily at high dose) may elevate and prolong serum levels of methotrexate and/or its metabolite hydroxymethotrexate, possibly leading to methotrexate toxicities. No formal drug interaction studies of methotrexate with PPIs have been conducted [see Warnings and Precautions (5.9)].
Intervention: | A temporary withdrawal of rabeprazole sodium delayed-release capsules may be considered in some patients receiving high-dose methotrexate administration.
Digoxin
Clinical Impact: | Potential for increased exposure of digoxin [see Clinical Pharmacology (12.3)].
Intervention: | Monitor digoxin concentrations. Dose adjustment of digoxin may be needed to maintain therapeutic drug concentrations. See prescribing information for digoxin.
Drugs Dependent on Gastric pH for Absorption (e.g., iron salts, erlotinib, dasatinib, nilotinib, mycophenolate mofetil, ketoconazole, itraconazole)
Clinical Impact: | Rabeprazole can reduce the absorption of other drugs due to its effect on reducing intragastric acidity.
Intervention: | Mycophenolate mofetil (MMF): Co-administration of PPIs in healthy subjects and in transplant patients receiving MMF has been reported to reduce the exposure to the active metabolite, mycophenolic acid (MPA), possibly due to a decrease in MMF solubility at an increased gastric pH. The clinical relevance of reduced MPA exposure on organ rejection has not been established in transplant patients receiving rabeprazole sodium delayed-release capsules and MMF. Use rabeprazole sodium delayed-release capsules with caution in transplant patients receiving MMF.
Intervention: | See the prescribing information for other drugs dependent on gastric pH for absorption.
Tacrolimus
Clinical Impact: | Potentially increased exposure of tacrolimus, especially in transplant patients who are intermediate or poor metabolizers of CYP2C19.
Intervention: | Monitor tacrolimus whole blood trough concentrations. Dose adjustment of tacrolimus may be needed to maintain therapeutic drug concentrations. See prescribing information for tacrolimus.
Interactions with Investigations of Neuroendocrine Tumors
Clinical Impact: | Serum chromogranin A (CgA) levels increase secondary to PPI-induced decreases in gastric acidity. The increased CgA level may cause false positive results in diagnostic investigations for neuroendocrine tumors.
Intervention: | Temporarily stop rabeprazole sodium delayed-release capsules treatment at least 14 days before assessing CgA levels and consider repeating the test if initial CgA levels are high. If serial tests are performed (e.g. for monitoring), the same commercial laboratory should be used for testing, as reference ranges between tests may vary.
Interaction with Secretin Stimulation Test
Clinical Impact: | Hyper-response in gastrin secretion in adults in response to secretin stimulation test, falsely suggesting gastrinoma.
Intervention: | Temporarily stop treatment with rabeprazole sodium delayed-release capsules at least 14 days before assessing to allow gastrin levels to return to baseline.
False Positive Urine Tests for THC
Clinical Impact: | There have been reports of false positive urine screening tests for tetrahydrocannabinol (THC) in patients receiving PPIs.
Intervention: | An alternative confirmatory method should be considered to verify positive results.

8 USE IN SPECIFIC POPULATIONS

8.1 Pregnancy

Risk Summary

There are no available human data on rabeprazole sodium delayed-release capsules use in pregnant women to inform the drug associated risk. The background risk of major birth defects and miscarriage for the indicated populations are unknown. However, the background risk in the U.S. general population of major birth defects is 2-4% and of miscarriage is 15-20% of clinically recognized pregnancies. No evidence of adverse developmental effects were seen in animal reproduction studies with rabeprazole administered during organogenesis at 13 and 8 times the human area under the plasma concentration-time curve (AUC) at the recommended dose for GERD, in rats and rabbits, respectively [see Data].

Changes in bone morphology were observed in offspring of rats treated with oral doses of a different PPI through most of pregnancy and lactation. When maternal administration was confined to gestation only, there were no effects on bone physeal morphology in the offspring at any age [see Data].

Data

Animal Data

Embryo-fetal developmental studies have been performed in rats at intravenous doses of rabeprazole during organogenesis up to 50 mg/kg/day (plasma AUC of 11.8 µg•hr/mL, about 13 times the adult human exposure at the recommended oral dose for GERD) and rabbits at intravenous doses up to 30 mg/kg/day (plasma AUC of 7.3 µg•hr/mL, about 8 times the adult human exposure at the recommended oral dose for GERD: 20 mg of rabeprazole delayed-release tablets per day) and have revealed no evidence of harm to the fetus due to rabeprazole.

Administration of rabeprazole to rats in late gestation and during lactation at an oral dose of 400 mg/kg/day (about 195 times the adult human oral dose based on mg/m^2) resulted in decreases in body weight gain of the pups.

A pre- and postnatal developmental toxicity study in rats with additional endpoints to evaluate bone development was performed with a different PPI at about 3.4 to 57 times an oral human dose on a body surface area basis. Decreased femur length, width and thickness of cortical bone, decreased thickness of the tibial growth plate, and minimal to mild bone marrow hypocellularity were noted at doses of this PPI equal to or greater than 3.4 times an oral human dose on a body surface area basis. Physeal dysplasia in the femur was also observed in offspring after in utero and lactational exposure to the PPI at doses equal to or greater than 33.6 times an oral human dose on a body surface area basis. Effects on maternal bone were observed in pregnant and lactating rats in a pre- and postnatal toxicity study when the PPI was administered at oral doses of 3.4 to 57 times an oral human dose on a body surface area basis. When rats were dosed from gestational day 7 through weaning on postnatal day 21, a statistically significant decrease in maternal femur weight of up to 14% (as compared to placebo treatment) was observed at doses equal to or greater than 33.6 times an oral human dose on a body surface area basis.

A follow-up developmental toxicity study in rats with further time points to evaluate pup bone development from postnatal day 2 to adulthood was performed with a different PPI at oral doses of 280 mg/kg/day (about 68 times an oral human dose on a body surface area basis) where drug administration was from either gestational day 7 or gestational day 16 until parturition. When maternal administration was confined to gestation only, there were no effects on bone physeal morphology in the offspring at any age.

8.2 Lactation

Risk Summary

Lactation studies have not been conducted to assess the presence of rabeprazole in human milk, the effects of rabeprazole on the breastfed infant, or the effects of rabeprazole on milk production. Rabeprazole is present in rat milk. The development and health benefits of breastfeeding should be considered along with the mother's clinical need for rabeprazole sodium delayed-release capsules and any potential adverse effects on the breastfed infant from rabeprazole sodium delayed-release capsules or from the underlying maternal condition.

8.4 Pediatric Use

GERD in Pediatric Patients 1 to 11 Years of Age

The use of rabeprazole sodium delayed-release capsules for treatment of GERD in pediatric patients 1 to 11 years of age is supported by a randomized, multicenter, double-blind clinical trial which evaluated two dose levels of rabeprazole sodium delayed-release capsules in 127 pediatric patients with endoscopic and histologic evidence of GERD prior to study treatment. Dosing was determined by body weight: Patients weighing 6.0 to 14.9 kg received either 5 or 10 mg of rabeprazole sodium delayed-release capsules daily and those weighing 15.0 kg or more received 10 or 20 mg of rabeprazole sodium delayed-release capsules daily. After 12 weeks of rabeprazole treatment, 81% of patients demonstrated esophageal mucosal healing on endoscopic assessment. In patients who had esophageal mucosal healing at 12 weeks and elected to continue for 24 more weeks of rabeprazole, 90% retained esophageal mucosal healing at 36 weeks. No prespecified formal hypothesis testing for evaluation of efficacy was conducted. The absence of a placebo group does not allow assessment of sustained efficacy through 36 weeks. There were no adverse reactions reported in this study that were not previously observed in adolescents or adults.

Symptomatic GERD in Infants 1 to 11 Months of Age

The use of rabeprazole sodium delayed-release capsules is not recommended because studies conducted do not demonstrate efficacy for the treatment of GERD in pediatric patients younger than 1 year of age.

In a randomized, multicenter, placebo-controlled withdrawal trial, infants 1 to 11 months of age with a clinical diagnosis of symptomatic GERD, or suspected or endoscopically proven GERD, were treated up to 8 weeks in two treatment periods. In the first treatment period (open-label), 344 infants received 10 mg of rabeprazole sodium delayed-release capsules for up to 3 weeks. Infants with clinical response were then eligible to enter the second treatment period, which was double-blind and randomized. Two hundred sixty-eight infants were randomized to receive either placebo or 5 mg or 10 mg rabeprazole sodium delayed-release capsules.

This study did not demonstrate efficacy based on assessment of frequency of regurgitation and weight-for-age Z-score. Adverse reactions that occurred in ≥5% of patients in any treatment group and with a higher rate than placebo included pyrexia (7%) and increased serum gastrin levels (5%). There were no adverse reactions reported in this study that were not previously observed in adolescents and adults.

Neonates <1 Month and Preterm Infants <44 Weeks Corrected Gestational Age

The use of rabeprazole sodium delayed-release capsules is not recommended for the treatment of GERD, based on the risk of prolonged acid suppression and lack of demonstrated safety and effectiveness in neonates. Based on population pharmacokinetic analysis, the median (range) for the apparent clearance (CL/F) was 1.05 L/h (0.0543 to 3.44 L/h) in neonates and 4.46 L/h (0.822 to 12.4 L/h) in patients 1 to 11 months of age following once daily administration of oral rabeprazole sodium delayed-release capsules.

Juvenile Animal Data

Studies in juvenile and young adult rats and dogs were performed. In juvenile animal studies rabeprazole sodium was administered orally to rats for up to 5 weeks and to dogs for up to 13 weeks, each commencing on Day 7 post-partum and followed by a 13-week recovery period. Rats were dosed at 5, 25, or 150 mg/kg/day and dogs were dosed at 3, 10, or 30 mg/kg/day. The data from these studies were comparable to those reported for young adult animals. Pharmacologically mediated changes, including increased serum gastrin levels and stomach changes, were observed at all dose levels in both rats and dogs. These observations were reversible over the 13-week recovery periods. Although body weights and/or crown-rump lengths were minimally decreased during dosing, no effects on the development parameters were noted in either juvenile rats or dogs.

When juvenile animals were treated for 28 days with a different PPI at doses equal to or greater than 34 times the daily oral human dose on a body surface area basis, overall growth was affected and treatment-related decreases in body weight (approximately 14%) and body weight gain, and decreases in femur weight and femur length were observed.

8.5 Geriatric Use

No studies with rabeprazole sodium delayed-release capsules have been conducted in geriatric patients. Rabeprazole sodium delayed-release capsules are not indicated for use in patients older than 11 years of age.

8.6 Hepatic Impairment

Administration of rabeprazole sodium delayed-release tablets to adult patients with mild to moderate hepatic impairment (Child-Pugh Class A and B, respectively) resulted in increased exposure and decreased elimination [see Clinical Pharmacology (12.3)]. No dosage adjustment of rabeprazole sodium delayed-release capsules is necessary in patients with mild to moderate hepatic impairment. There is no information in patients with severe hepatic impairment (Child-Pugh Class C). Avoid use of rabeprazole sodium delayed-release capsules in patients with severe hepatic impairment; however, if treatment is necessary, monitor patients for adverse reactions [see Warnings and Precautions (5), Adverse Reactions (6)].

10 OVERDOSAGE

Seven reports of accidental overdosage with rabeprazole have been received. The maximum reported overdose was 80 mg. There were no clinical signs or symptoms associated with any reported overdose. Patients with Zollinger-Ellison syndrome have been treated with up to 120 mg rabeprazole once daily. No specific antidote for rabeprazole is known. Rabeprazole is extensively protein bound and is not readily dialyzable.

In the event of overdosage, treatment should be symptomatic and supportive.

If over-exposure occurs, call your Poison Control Center at 1-800-222-1222 for current information on the management of poisoning or overdosage.

11 DESCRIPTION

The active ingredient in rabeprazole sodium delayed-release capsules is rabeprazole sodium, which is a proton pump inhibitor. It is a substituted benzimidazole known chemically as 2-[[[4-(3-methoxypropoxy)-3-methyl-2-pyridinyl]-methyl]sulfinyl]-1H–benzimidazole sodium salt. It has an empirical formula of C18H20N3NaO3S and a molecular weight of 381.42. Rabeprazole sodium is a white to slightly yellowish-white solid. It is very soluble in water and methanol, freely soluble in ethanol, chloroform, and ethyl acetate and insoluble in ether and n-hexane. The stability of rabeprazole sodium is a function of pH; it is rapidly degraded in acid media, and is more stable under alkaline conditions. The structural figure is:

Figure 1

Rabeprazole sodium delayed-release capsules (sprinkle) are available for oral administration as 10 mg rabeprazole sodium delayed-release capsules containing enteric coated granules.

Rabeprazole sodium delayed-release capsules contain granules of rabeprazole sodium in a hard hypromellose capsule. Inactive ingredients are colloidal silicon dioxide, diacetylated monoglycerides, ethylcellulose, hydroxypropyl cellulose, hypromellose phthalate, magnesium oxide, magnesium stearate, mannitol, talc, titanium dioxide, carrageenan, potassium chloride, FD&C Yellow, No. 6 (in the 10 mg capsule), and gray printing ink.

12 CLINICAL PHARMACOLOGY

12.1 Mechanism of Action

Rabeprazole belongs to a class of antisecretory compounds (substituted benzimidazole proton-pump inhibitors) that do not exhibit anticholinergic or histamine H2-receptor antagonist properties, but suppress gastric acid secretion by inhibiting the gastric H^+, K^+ATPase at the secretory surface of the gastric parietal cell. Because this enzyme is regarded as the acid (proton) pump within the parietal cell, rabeprazole has been characterized as a gastric proton-pump inhibitor. Rabeprazole blocks the final step of gastric acid secretion.

In gastric parietal cells, rabeprazole is protonated, accumulates, and is transformed to an active sulfenamide. When studied in vitro, rabeprazole is chemically activated at pH 1.2 with a half-life of 78 seconds. It inhibits acid transport in porcine gastric vesicles with a half-life of 90 seconds.

12.3 Pharmacokinetics

Absorption

After oral administration to healthy adults of 10 mg rabeprazole sodium delayed-release capsules (delayed-release capsules opened and granules sprinkled on one tablespoon [15 mL] of applesauce) under fasting condition, median time (Tmax) to peak plasma concentrations (Cmax) of rabeprazole was 2.5 hours and ranged 1.0 to 6.5 hours. The plasma half-life of rabeprazole ranges from 1 to 2 hours.

In healthy adults, a concomitant high fat meal delayed the absorption of rabeprazole from rabeprazole sodium delayed-release capsules (granules sprinkled on one tablespoon (15 mL) of applesauce) resulting in the median Tmax of 4.5 hours and decreased the Cmax and AUClast on average by 55% and 33%, respectively [see Dosage and Administration (2.2)].

When 10 mg rabeprazole sodium delayed-release capsules (granules) administered under fasting conditions to healthy adults on one tablespoon (15 mL) of applesauce, one tablespoon (15 mL) of yogurt, or when mixed with a small amount (5 mL) of liquid infant formula; the type of soft food did not significantly affect Tmax, Cmax and AUC of rabeprazole.

Distribution

Rabeprazole is 96.3% bound to human plasma proteins.

Elimination

Metabolism: Rabeprazole is extensively metabolized. A significant portion of rabeprazole is metabolized via systemic nonenzymatic reduction to a thioether compound. Rabeprazole is also metabolized to sulphone and desmethyl compounds via cytochrome P450 in the liver. The thioether and sulphone are the primary metabolites measured in human plasma. These metabolites were not observed to have significant antisecretory activity. In vitro studies have demonstrated that rabeprazole is metabolized in the liver primarily by cytochromes P450 3A (CYP3A) to a sulphone metabolite and cytochrome P450 2C19 (CYP2C19) to desmethyl rabeprazole. CYP2C19 exhibits a known genetic polymorphism due to its deficiency in some sub-populations (e.g., 3 to 5% of Caucasians and 17 to 20% of Asians). Rabeprazole metabolism is slow in these sub-populations, therefore, they are referred to as poor metabolizers of the drug.

Excretion: Following a single 20 mg oral dose of ^14C-labeled rabeprazole, approximately 90% of the drug was eliminated in the urine, primarily as thioether carboxylic acid; its glucuronide, and mercapturic acid metabolites. The remainder of the dose was recovered in the feces. Total recovery of radioactivity was 99.8%. No unchanged rabeprazole was recovered in the urine or feces.

Specific Populations

Pediatric Patients: In patients with GERD 1 to 11 years of age, following once daily administration of rabeprazole sodium delayed-release capsules at doses from 0.14 to 1 mg/kg, the median time to peak plasma concentration ranged from 2 to 4 hours and the half-life was about 2.5 hours. No appreciable accumulation was noted following 5 days of dosing compared to exposure after a single dose.

Based on population pharmacokinetic analysis, over the body weight range from 7 to 77 kg, the apparent rabeprazole clearance increased from 8.0 to 13.5 L/hr, an increase of 69%.

The mean estimated total exposure i.e., AUC after a 10 mg dose of rabeprazole sodium delayed-release capsules in patients with GERD 1 to 11 years of age is comparable to AUC after 10 mg rabeprazole sodium delayed-release tablet in adults.

Male and Female Patients and Racial or Ethnic Groups: In analyses of adult data adjusted for body mass and height, rabeprazole pharmacokinetics showed no clinically significant differences between male and female subjects. In studies that used different formulations of rabeprazole, AUC0-∞ values for healthy Japanese men were approximately 50 to 60% greater than values derived from pooled data from healthy men in the United States.

Patients with Renal Impairment: In 10 adult patients with stable end-stage renal disease requiring maintenance hemodialysis (creatinine clearance ≤5 mL/min/1.73 m^2), no clinically significant differences were observed in the pharmacokinetics of rabeprazole after administration of rabeprazole 20 mg delayed-release tablets when compared to 10 healthy adult subjects.

Patients with Hepatic Impairment: In a single dose study of 10 adult patients with chronic mild to moderate hepatic impairment (Child-Pugh Class A and B, respectively) who were administered a 20 mg dose of rabeprazole sodium delayed-release tablets, AUC0-24 was approximately doubled, the elimination half-life was 2- to 3-fold higher, and total body clearance was decreased to less than half compared to values in healthy adult men.

In a multiple dose study of 12 adult patients with mild to moderate hepatic impairment administered 20 mg rabeprazole sodium delayed-release tablets once daily for eight days, AUC0-∞ and Cmax values increased approximately 20% compared to values in healthy age- and gender-matched subjects. These increases were not statistically significant.

No information exists on rabeprazole disposition in patients with severe hepatic impairment (Child-Pugh Class C) [see Use in Specific Populations (8.6)].

Drug Interaction Studies

Effects of Other Drugs on Rabeprazole

Antacids: Co-administration of rabeprazole sodium delayed-release tablets and antacids produced no clinically relevant changes in plasma rabeprazole concentrations.

Effects of Rabeprazole on Other Drugs

Studies in healthy adult subjects have shown that rabeprazole does not have clinically significant interactions with other drugs metabolized by the CYP450 system, such as theophylline (CYP1A2) given as single oral doses, diazepam (CYP2C9 and CYP3A4) as a single intravenous dose, and phenytoin (CYP2C9 and CYP2C19) given as a single intravenous dose (with supplemental oral dosing). Steady state interactions of rabeprazole and other drugs metabolized by this enzyme system have not been studied in patients.

Clopidogrel: Clopidogrel is metabolized to its active metabolite in part by CYP2C19. A study of healthy adult subjects including CYP2C19 extensive and intermediate metabolizers receiving once daily administration of clopidogrel 75 mg concomitantly with placebo or with 20 mg rabeprazole sodium delayed-release tablets (n=36), for 7 days was conducted. The mean AUC of the active metabolite of clopidogrel was reduced by approximately 12% (mean AUC ratio was 88%, with 90% CI of 81.7 to 95.5%) when rabeprazole sodium delayed-release tablets was co-administered compared to administration of clopidogrel with placebo [see Drug Interactions (7)].

Digoxin: In healthy adult subjects (n=16), co-administration of 20 mg rabeprazole sodium delayed-release tablets with 2.5 mg once daily doses of digoxin at steady state resulted in approximately 29% and 19% increase in mean Cmax and AUC(0-24) of digoxin [see Drug Interactions (7)].

Ketoconazole: In healthy adult subjects (n=19), co-administration of 20 mg rabeprazole sodium delayed-release tablets at steady state with a single 400 mg oral dose ketoconazole resulted in approximately an average of 31% reduction in both Cmax and AUC(0-inf) of ketoconazole [see Drug Interactions (7)].

Cyclosporine: In vitro incubations employing human liver microsomes indicated that rabeprazole inhibited cyclosporine metabolism with an IC50 of 62 micromolar, a concentration that is over 50 times higher than the Cmax in healthy volunteers following 14 days of dosing with 20 mg of rabeprazole sodium delayed-release tablets. This degree of inhibition is similar to that by omeprazole at equivalent concentrations.

12.5 Pharmacogenomics

In a clinical study in Japan evaluating rabeprazole sodium delayed-release tablets in Japanese adult patients categorized by CYP2C19 genotype (n=6 per genotype category), gastric acid suppression was higher in poor metabolizers as compared to extensive metabolizers. The clinical relevance of this is not known. This could be due to higher rabeprazole plasma levels in poor metabolizers. Whether or not interactions of rabeprazole sodium with other drugs metabolized by CYP2C19 would be different between extensive metabolizers and poor metabolizers has not been studied.

13 NONCLINICAL TOXICOLOGY

13.1 Carcinogenesis, Mutagenesis, Impairment of Fertility

In an 88/104-week carcinogenicity study in CD-1 mice, rabeprazole at oral doses up to 100 mg/kg/day did not produce any increased tumor occurrence. The highest tested dose produced a systemic exposure to rabeprazole (AUC) of 1.40 µg•hr/mL which is 1.6 times the adult human exposure (plasma AUC0-∞ = 0.88 µg•hr/mL) at the recommended dose for GERD (20 mg of rabeprazole sodium delayed-release tablets per day). In a 28-week carcinogenicity study in p53+/- transgenic mice, rabeprazole at oral doses of 20, 60, and 200 mg/kg/day did not cause an increase in the incidence rates of tumors but produced gastric mucosal hyperplasia at all doses. The systemic exposure to rabeprazole at 200 mg/kg/day is about 17 to 24 times the adult human exposure at the recommended dose for GERD (20 mg of rabeprazole sodium delayed-release tablets per day). In a 104-week carcinogenicity study in Sprague-Dawley rats, males were treated with oral doses of 5, 15, 30, and 60 mg/kg/day and females with 5, 15, 30, 60, and 120 mg/kg/day. Rabeprazole produced gastric enterochromaffin-like (ECL) cell hyperplasia in male and female rats and ECL cell carcinoid tumors in female rats at all doses including the lowest tested dose. The lowest dose (5 mg/kg/day) produced a systemic exposure to rabeprazole (AUC) of about 0.1 µg•hr/mL which is about 0.1 times the adult human exposure at the recommended dose for GERD (20 mg of rabeprazole sodium delayed-release tablets per day). In male rats, no treatment-related tumors were observed at doses up to 60 mg/kg/day producing a rabeprazole plasma exposure (AUC) of about 0.2 µg•hr/mL (0.2 times the adult human exposure at the recommended dose for GERD).

Rabeprazole was positive in the Ames test, the Chinese hamster ovary cell (CHO/HGPRT) forward gene mutation test, and the mouse lymphoma cell (L5178Y/TK+/–) forward gene mutation test. Its demethylated-metabolite was also positive in the Ames test. Rabeprazole was negative in the in vitro Chinese hamster lung cell chromosome aberration test, the in vivo mouse micronucleus test, and the in vivo and ex vivo rat hepatocyte unscheduled DNA synthesis (UDS) tests.

Rabeprazole at intravenous doses up to 30 mg/kg/day (plasma AUC of 8.8 µg•hr/mL, about 10 times the adult human exposure at the recommended dose for GERD) was found to have no effect on fertility and reproductive performance of male and female rats. The recommended dose for GERD in adults is 20 mg per day (rabeprazole sodium delayed-release tablets).

14 CLINICAL STUDIES

The use of rabeprazole sodium delayed-release capsules in pediatric patients 1 to 11 years of age is supported by a two-part, multicenter, randomized, double-blind, parallel 2 dose arms clinical trial which was conducted in 127 pediatric patients with endoscopic and histologic evidence of GERD prior to study treatment.

Part 1 of the trial was 12 weeks in duration. Patients were randomized to one of two rabeprazole dose levels based on body weight. Patients weighing 6 to 14.9 kg received either 5 or 10 mg rabeprazole sodium delayed-release capsules, and those with body weight ≥15 kg received 10 mg rabeprazole sodium delayed-release capsules. Part 2 was a 24-week double-blinded extension of Part 1 (on same dose assigned in Part 1). Endoscopic evaluations were performed at 12 weeks (Part 1) and 36 weeks (Part 2) to assess esophageal healing. No prespecified formal hypothesis testing was conducted.

For Part 1, rates of endoscopic healing were calculated and are shown in Table 3.

Table 3: Short-Term (12-Week) Healing Rates In 1 To 11 Year Old Children (Part 1)
Endoscopic Classification of GERD At Baseline | Healing Rate at 12 weeks
Endoscopic Classification of GERD At Baseline | Body Weight Less than 15 kg |  | Body Weight 15 kg or Greater
 | 5 mg dose | 10 mg dose | 10 mg dose
Erosivea | 88% (7/8) | 83% (5/6) | 71% (12/17)
Non-erosiveb | 78% (7/9) | 100% (10/10) | 81% (17/21)
a Hetzel-Dent score ≥2
b Hetzel-Dent score = 1

Of the 87 patients with healing in Part 1, 64 patients were enrolled into Part 2. The absence of a placebo group does not allow assessment of sustained efficacy through 36 weeks. Of the 52 patients with available data, healing was observed in 47 (90%) patients at 36 weeks.

The recommended dosage of rabeprazole sodium delayed-release capsules is 5 mg once daily for 12 weeks in patients less than 15 kg with the option to increase to 10 mg once daily if there is an inadequate response. In patients 15 kg or greater, the recommended dosage is 10 mg once daily for 12 weeks.

16 HOW SUPPLIED/STORAGE AND HANDLING

Rabeprazole sodium delayed-release capsules (10 mg) (sprinkle) are supplied as transparent yellow and opaque white capsules containing enteric coated granules. Identification and strength (ACX 10mg) are imprinted on the body of the capsule. An arrow (↑) imprint on the capsule cap indicates direction for opening a capsule.

Bottles of 30 (NDC 72834-210-30)

STORAGE AND HANDLING

Store at 25°C (77°F); excursions permitted to 15-30°C (59-86°F) [see USP Controlled Room Temperature]. Protect from moisture.

17 PATIENT COUNSELING INFORMATION

Advise the patient or caregiver to read the FDA-approved patient labeling (Medication Guide).

Acute Interstitial Nephritis

Advise the patient or caregiver to call the patient’s healthcare provider immediately if they experience signs and/or symptoms associated with acute interstitial nephritis [see Warnings and Precautions (5.3)].

Clostridium difficile-Associated Diarrhea

Advise the patient or caregiver to immediately call the patient’s healthcare provider if they experience diarrhea that does not improve [see Warnings and Precautions (5.4)].

Bone Fracture

Advise the patient or caregiver to report any fractures, especially of the hip, wrist or spine, to the patient’s healthcare provider [see Warnings and Precautions (5.5)].

Cutaneous and Systemic Lupus Erythematosus

Advise the patient or caregiver to immediately call the patient’s healthcare provider for any new or worsening of symptoms associated with cutaneous or systemic lupus erythematosus [see Warnings and Precautions (5.6)]

Cyanocobalamin (Vitamin B-12) Deficiency

Advise the patient or caregiver to report any clinical symptoms that may be associated with cyanocobalamin deficiency to the patient’s healthcare provider if they have been receiving rabeprazole sodium delayed-release capsules for longer than 3 years [see Warnings and Precautions (5.7)].

Hypomagnesemia

Advise the patient or caregiver to report any clinical symptoms that may be associated with hypomagnesemia to the patient’s healthcare provider, if they have been receiving rabeprazole sodium delayed-release capsules for at least 3 months [see Warnings and Precautions (5.8)].

Drug Interactions

Advise the patient or caregiver to report to the patient’s healthcare provider if they are taking rilpilvirine-containing products [see Contraindications (4)], warfarin or high-dose methotrexate [see Warnings and Precautions (5.2, 5.9)].

Administration

- Take the dose 30 minutes before a meal.
- Do not swallow the capsule whole.
- Open the rabeprazole sodium delayed-release capsule and sprinkle the granule contents on a small amount of soft food (e.g., applesauce, fruit or vegetable based baby food, or yogurt) or empty contents into a small amount of liquid (e.g., infant formula, apple juice, or pediatric electrolyte solution). Food or liquid should be at or below room temperature.
- Do not chew or crush the granules.
- Take the entire dose within 15 minutes of preparation.
- Do not store mixture for future use.
- Take a missed dose as soon as possible. If it is almost time for the next dose, skip the missed dose and go back to the normal schedule. Do not take 2 doses at the same time.

Distributed and Marketed by Sarras Health, LLC, Athens, GA 30601

MEDICATION GUIDE
Rabeprazole Sodium Delayed Release Capsules (Sprinkle)

What is the most important information I should know about rabeprazole sodium delayed-release capsules?
Your child should take rabeprazole sodium delayed-release capsules exactly as prescribed, at the lowest dose possible and for the shortest time needed.
Rabeprazole sodium delayed-release capsules may help your child's acid-related symptoms, but your child could still have serious stomach problems. Talk with your child's doctor.
Rabeprazole sodium delayed-release capsules can cause serious side effects, including:

- A type of kidney problem (acute interstitial nephritis). Some people who take proton pump inhibitor (PPI) medicines, including rabeprazole sodium delayed-release capsules, may develop a kidney problem called acute interstitial nephritis that can happen at any time during treatment with rabeprazole sodium delayed-release capsules. Call your child’s doctor right away if your child has a decrease in the amount that they urinate or if they have blood in their urine.
- Diarrhea caused by an infection (Clostridium difficile) in your child’s intestines. Call your child’s doctor right away if your child has watery stools or stomach pain that does not go away. Your child may or may not have a fever.
- Bone fractures (hip, wrist or spine). Bone fractures in the hip, wrist or spine may happen in people who take multiple daily doses of PPI medicines and for a long period of time (a year or longer). Tell your child’s doctor if your child has a bone fracture, especially in the hip, wrist or spine.
- Certain types of lupus erythematosus. Lupus erythematosus is an autoimmune disorder (the body’s immune cells attack other cells or organs in the body). Some people who take PPI medicines, including rabeprazole sodium delayed-release capsules, may develop certain types of lupus erythematosus or have worsening of the lupus they already have. Call your child’s doctor right away if they have new or worsening joint pain or a rash on their cheeks or arms that gets worse in the sun.

Talk to your child’s doctor about your child’s risk of serious side effects.
Rabeprazole sodium delayed-release capsules can have other serious side effects. See "What are the possible side effects of rabeprazole sodium delayed-release capsules?"

What are rabeprazole sodium delayed-release capsules?
Rabeprazole sodium delayed-release capsules are a prescription medicine called a proton pump inhibitor (PPI). Rabeprazole sodium delayed-release capsules reduce the amount of acid in the stomach.
Rabeprazole sodium delayed-release capsules are used in children 1 year to 11 years of age to treat Gastroesophageal Reflux Disease (GERD) for up to 12 weeks.
Rabeprazole sodium delayed-release capsules are not effective in treating GERD in children under 1 year of age.
Rabeprazole sodium delayed-release capsules should not be used to treat GERD in babies younger than 1 month of age.

Your child should not take rabeprazole sodium delayed-release capsules if they are:

- allergic to rabeprazole, any other PPI medicine, or any of the ingredients in rabeprazole sodium delayed-release capsules. See the end of this Medication Guide for a complete list of ingredients.
- taking a medicine that contains rilpivirine (EDURANT, COMPLERA, ODEFSEY) used to treat HIV-1 (Human Immunodeficiency Virus).

Before your child takes rabeprazole sodium delayed-release capsules, tell your child’s doctor about all of your child’s medical conditions, including if they:

- have low magnesium levels in their blood.
- have liver problems.
- are pregnant or plan to become pregnant. It is not known if rabeprazole sodium delayed-release capsules can harm an unborn baby.
- are breastfeeding or plan to breastfeed. It is not known if rabeprazole sodium delayed-release capsules passes into breast milk. Talk to your child’s doctor about the best way to feed her baby if she takes rabeprazole sodium delayed-release capsules.

Tell your child’s doctor about all the medicines your child takes, including prescription and over-the-counter medicines, vitamins, and herbal supplements. Especially tell your child’s doctor if your child takes warfarin (COUMADIN, JANTOVEN) or methotrexate (Otrexup, Rasuvo,Trexall, Xatmep).

How should my child take rabeprazole sodium delayed-release capsules?

- Your child should take rabeprazole sodium delayed-release capsules exactly as prescribed. Your child’s doctor will prescribe the dose that is right for your child.
- Your child should take rabeprazole sodium delayed-release capsules 1 time each day.
- Your child should take rabeprazole sodium delayed-release capsules 30 minutes before a meal.
- Your child should not swallow the rabeprazole sodium delayed-release capsule whole.
- Prepare and give a dose of rabeprazole sodium delayed-release capsules to your child as follows:
  - Open the rabeprazole sodium delayed-release capsule in the direction that the arrow (↑) on the capsule is pointing. Sprinkle all of the capsule contents onto a small amount of soft food such as applesauce, fruit or vegetable based baby food, or yogurt. You may also empty all of the capsule contents into a small amount of infant formula, apple juice, or a pediatric electrolyte solution. The food or liquid that you use should be at or below room temperature.
  - Your child should swallow the entire mixture. They should not chew or crush the granules.
  - Your child should take the entire dose within 15 minutes of preparing it. Do not save it for use later.
- If your child misses a dose of rabeprazole sodium delayed-release capsules, they should take it as soon as possible. If it is almost time for their next dose, they should not take the missed dose. Your child should take their next dose at their regular time. They should not take 2 doses at the same time.
- If your child takes too much rabeprazole sodium delayed-release capsules, call your child’s doctor or your poison control center at 1-800-222-1222 right away, or go to the nearest emergency room.

What are the possible side effects of rabeprazole sodium delayed-release capsules?
Rabeprazole sodium delayed-release capsules can cause serious side effects, including:

- See "What is the most important information I should know about rabeprazole sodium delayed-release capsules?"
- Interaction with warfarin. Taking warfarin with a PPI medicine may lead to an increased risk of bleeding and death. If your child takes warfarin, their doctor may check their blood to see if they have an increased risk of bleeding. If your child takes warfarin during treatment with rabeprazole sodium delayed-release capsules, tell their doctor right away if they have any signs or symptoms of bleeding, including:

-
  - pain, swelling or discomfort
  - headaches, dizziness, or weakness
  - unusual bruising (bruises that happen without known cause or that grow in size)
  - nosebleeds
  - bleeding gums
  - bleeding from cuts takes a long time to stop

-
  - menstrual bleeding that is heavier than normal
  - pink or brown urine
  - red or black stools
  - coughing up blood
  - vomiting blood or vomit that looks like coffee grounds

- Low vitamin B-12 levels in the body can happen in people who have taken rabeprazole sodium delayed-release capsules for a long time (more than 3 years). Tell your child’s doctor if your child has symptoms of low vitamin B-12 levels, including shortness of breath, lightheadedness, irregular heartbeat, muscle weakness, pale skin, feeling tired, mood changes, and tingling or numbness in the arms and legs.
- Low magnesium levels in the body can happen in people who have taken rabeprazole sodium delayed-release capsules for at least 3 months. Tell your child’s doctor if your child has symptoms of low magnesium levels, including seizures, dizziness, irregular heartbeat, jitteriness, muscle aches or weakness, and spasms of hands, feet or voice.
- Stomach growths (fundic gland polyps). People who take PPI medicines for a long time have an increased risk of developing a certain type of stomach growths called fundic gland polyps, especially after taking PPI medicines for more than 1 year.

The most common side effects of rabeprazole sodium delayed-release capsules include: vomiting, stomach-area (abdomen) pain, diarrhea, headache, and nausea.
These are not all of the possible side effects of rabeprazole sodium delayed-release capsules. Call your child’s doctor for medical advice about side effects. You may report side effects to FDA at 1-800-FDA-1088.

How should I store rabeprazole sodium delayed-release capsules?
Store rabeprazole sodium delayed-release capsules in a dry place at room temperature between 68°F to 77°F (20°C to 25°C).
Keep rabeprazole sodium delayed-release capsules and all medicines out of the reach of children.

General Information about the safe and effective use of rabeprazole sodium delayed-release capsules.
Medicines are sometimes prescribed for purposes other than those listed in a Medication Guide. Do not use rabeprazole sodium delayed-release capsules for a condition for which it was not prescribed. Do not give rabeprazole sodium delayed-release capsules to other people, even if they have the same symptoms that you have. It may harm them.
You can ask your child's doctor or pharmacist for information about rabeprazole sodium delayed-release capsules that is written for health professionals.

What are the ingredients in rabeprazole sodium delayed-release capsules?
Active ingredient: rabeprazole sodium
Inactive ingredients: colloidal silicon dioxide, diacetylated monoglycerides, ethylcellulose, hydroxypropyl cellulose, hypromellose phthalate, magnesium oxide, magnesium stearate, mannitol, talc, titanium dioxide, carrageenan, potassium chloride, FD&C Yellow, No. 6 (in the 10 mg capsule), and gray printing ink.
Distributed and Marketed by Sarras Health, LLC
Athens, GA 30601

This Medication Guide has been approved by the U.S. Food and Drug Administration.

Revised: April 2019

PRINCIPAL DISPLAY PANEL - 10 mg Bottle Label

NDC: 72834-210-30

Rx only

Rabeprazole
Sodium Delayed
Release Capsules
(Sprinkle)

sarras health

10 mg

30 capsules